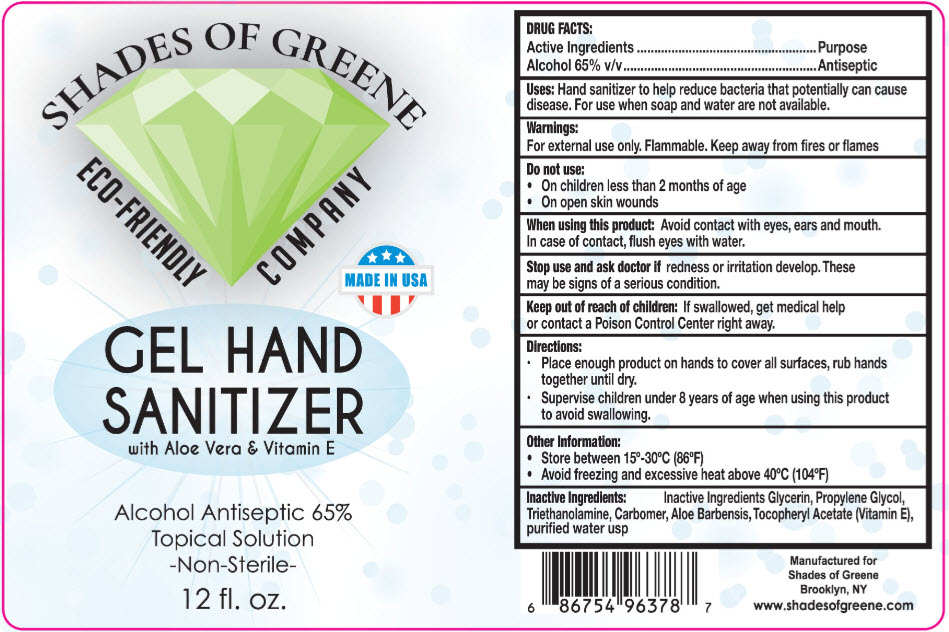 DRUG LABEL: Shades of Green 
NDC: 79626-001 | Form: GEL
Manufacturer: Shades of Green
Category: otc | Type: HUMAN OTC DRUG LABEL
Date: 20200810

ACTIVE INGREDIENTS: Alcohol 65 mL/100 mL
INACTIVE INGREDIENTS: Water; Glycerin; Aloe; .ALPHA.-TOCOPHEROL ACETATE; TROLAMINE; CARBOMER HOMOPOLYMER, UNSPECIFIED TYPE

Shades of Green Hand Sanitizer

DRUG FACTS:

Active Ingredients

Alcohol 65% v/v

Purpose

Antiseptic

Uses

Hand sanitizer to help reduce bacteria that potentially can cause disease. For use when soap and water are not available.

Warnings

For external use only. Flammable. Keep away from fires or flames

Do not use

- On children less than 2 months of age
- On open skin wounds

When using this product

Avoid contact with eyes, ears and mouth. In case of contact, flush eyes with water.

Stop use and ask doctor if redness or irritation develop. These may be signs of a serious condition.

Keep out of reach of children: If swallowed, get medical help or contact a Poison Control Center right away.

Directions

- Place enough product on hands to cover all surfaces, rub hands together until dry.
- Supervise children under 8 years of age when using this product to avoid swallowing.

Other Information

- Store between 15°-30°C (86°F)
- Avoid freezing and excessive heat above 40°C (104°F)

Inactive Ingredients

Inactive Ingredients Glycerin, Propylene Glycol, Triethanolamine, Carbomer, Aloe Barbensis, Tocopheryl Acetate (Vitamin E), purified water usp

PRINCIPAL DISPLAY PANEL - 12 fl. oz. Bottle Label

SHADES OF GREENE

ECO-FRIENDLY COMPANY

MADE IN USA

GEL HAND
SANITIZER
with Aloe Vera & Vitamin E

Alcohol Antiseptic 65%
Topical Solution
Non-Sterile

12 fl. oz.